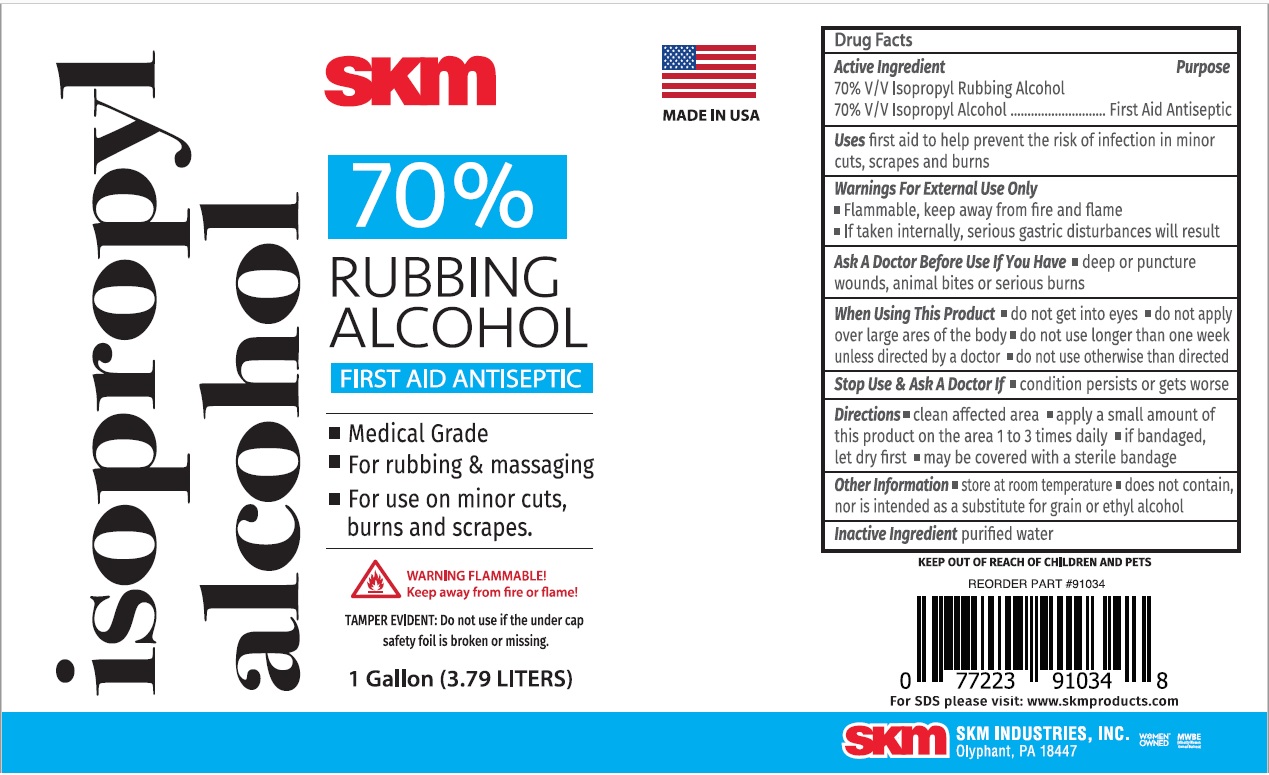 DRUG LABEL: SKM 70% Rubbing Alcohol
NDC: 74990-700 | Form: LIQUID
Manufacturer: Skm Industries Inc.
Category: otc | Type: HUMAN OTC DRUG LABEL
Date: 20210108

ACTIVE INGREDIENTS: ISOPROPYL ALCOHOL 70 mL/100 mL
INACTIVE INGREDIENTS: WATER

skm 70% RUBBING ALCOHOL FIRST AID ANTISEPTIC

Active Ingredient

70% V/V Isopropyl Rubbing Alcohol

70% V/V Isopropyl Alcohol

Purpose

First Aid Antiseptic

Uses

first aid to help prevent the risk of infection in minor cuts, scrapes and burns

Warnings For External Use Only

• Flammable, keep away from fire and flame

• If taken internally, serious gastric disturbances will result

Ask A Doctor Before Use If You Have • deep or puncture wounds, animal bites or serious burns

When Using This Product • do not get into eyes • do not apply over large areas of the body • do not use longer than one week unless directed by a doctor • do not use otherwise than directed

Stop Use & Ask A Doctor If • condition persists or gets worse

KEEP OUT OF REACH OF CHILDREN AND PETS

Directions

• clean affected area • apply a small amount of this product on the area 1 to 3 times daily • if bandaged, let dry first • may be covered with a sterile bandage

Other Information

• store at room temperature • does not contain, nor is intended as a substitute for grain or ethyl alcohol

Inactive Ingredient

purified water

• Medical Grade

• For rubbing & massaging

• For use on minor cuts, burns and scrapes.

WARNING FLAMMABLE!

Keep away from fire and flame!

TAMPER EVIDENT: Do not use if the under cap safety foil is broken or missing.

MADE IN USA

For SDS please visit: www.skmproducts.com

SKM INDUSTRIES, INC.

Olyphant, PA 18447

WOMEN OWNED™

MWBE (Minority Women Owned Business)